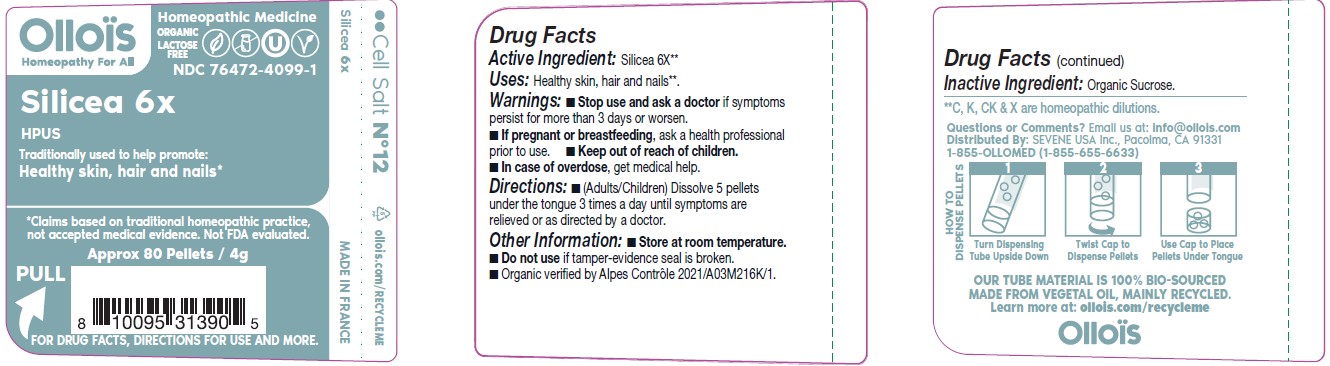 DRUG LABEL: SILICEA

NDC: 76472-4099 | Form: PELLET
Manufacturer: SEVENE USA
Category: homeopathic | Type: HUMAN OTC DRUG LABEL
Date: 20250211

ACTIVE INGREDIENTS: SILICON DIOXIDE 6 [hp_X]/1 1
INACTIVE INGREDIENTS: SUCROSE

Sevene USA (as PLD) - SILICEA 6X (76472-4099)

ACTIVE INGREDIENT:

SILICEA 6X**.

**C, K, CK & X are homeopathic dilutions.

TRADITIONALLY USE TO HELP PROMOTE:

Healthy skin, hair and nails*

*Claims based on traditional homeopathic practice, not accepted medical evidence. Not FDA evaluated

DIRECTIONS:

- (adults/children) Dissolve 5 pellets under the tongue 3 times a day until symptoms are relieved or as directed by a physician.

USES:

Healthy skin, hair and nails**.

WARNINGS:

- Stop use and ask a doctor if symptoms persist for more than 3 days or worsen.

PREGNANCY OR BREAST FEEDING

- If pregnant or breast-feeding, ask a health professional prior to use.

- Keep out of reach of children.
- In case of overdose, get medical help.

OTHER INFORMATION:

- Store at room temperature.
- Do not use if tamper-evidence seal is broken.
- Organic verified by Alpes Contrôle 2021/A03M216K/1.

INACTIVE INGREDIENT:

Organic Sucrose.

QUESTIONS OR COMMENTS?

Email us at: info@ollois.com